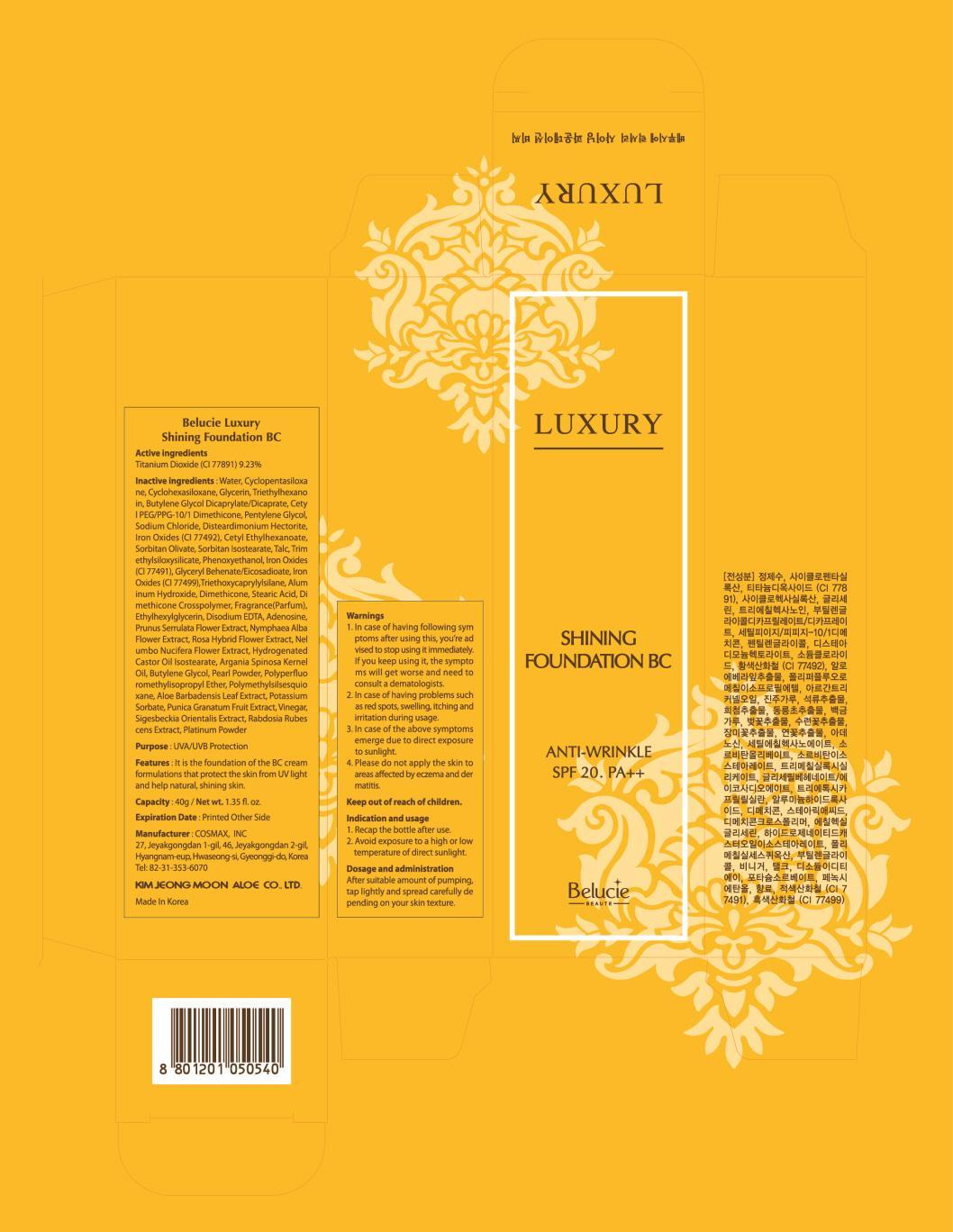 DRUG LABEL: Belucie Luxury Shinning Foundation BC
NDC: 50410-090 | Form: CREAM
Manufacturer: Kimjeongmoon Aloe Co., Ltd.
Category: otc | Type: HUMAN OTC DRUG LABEL
Date: 20150225

ACTIVE INGREDIENTS: Titanium Dioxide 3.69 g/40 g
INACTIVE INGREDIENTS: Water; Glycerin

ACTIVE INGREDIENT

Active ingredients: Titanium Dioxide (CI 77891) 9.23%

INACTIVE INGREDIENT

Inactive ingredients: Water, Cyclopentasiloxane, Cyclohexasiloxane, Glycerin, Triethylhexanoin, Butylene Glycol Dicaprylate/Dicaprate, Cetyl PEG/PPG-10/1 Dimethicone, Pentylene Glycol, Sodium Chloride, Disteardimonium Hectorite, Iron Oxides (CI 77492), Cetyl Ethylhexanoate, Sorbitan Olivate, Sorbitan Isostearate, Talc, Trimethylsiloxysilicate, Phenoxyethanol, Iron Oxides (CI 77491), Glyceryl Behenate/Eicosadioate, Iron Oxides (CI 77499), Triethoxycaprylylsilane, Aluminum Hydroxide, Dimethicone, Stearic Acid, Dimethicone Crosspolymer, Fragrance(Parfum), Ethylhexylglycerin, Disodium EDTA, Adenosine, Prunus Serrulata Flower Extract, Nymphaea Alba Flower Extract, Rosa Hybrid Flower Extract, Nelumbo Nucifera Flower Extract, Hydrogenated Castor Oil Isostearate, Argania Spinosa Kernel Oil, Butylene Glycol, Pearl Powder, Polyperfluoromethylisopropyl Ether, Polymethylsilsesquioxane, Aloe Barbadensis Leaf Extract, Potassium Sorbate, Punica Granatum Fruit Extract, Vinegar, Sigesbeckia Orientalis Extract, Rabdosia Rubescens Extract, Platinum Powder

PURPOSE

Purpose: UVA/UVB Protection

WARNINGS

Warnings: 1. In case of having following symptoms after using this, you’re advised to stop using it immediately. If you keep using it, the symptoms will get worse and need to consult a dematologists. 2. In case of having problems such as red spots, swelling, itching and irritation during usage 3. In case of the above symptoms emerge due to direct exposure to sunlight 4. Please do not apply the skin to areas affected by eczema and dermatitis

KEEP OUT OF REACH OF CHILDREN

INDICATIONS & USAGE

Indication and usage: 1. Recap the bottle after use. 2. Avoid exposure to a high or low temperature of direct sunlight

DOSAGE & ADMINISTRATION

Dosage and administration: After suitable amount of pumping, tap lightly and spread carefully depending on your skin texture.

PACKAGE LABEL.PRINCIPAL DISPLAY PANEL

Image of carton